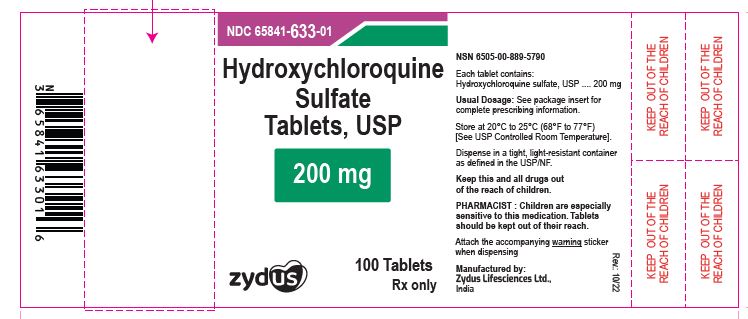 DRUG LABEL: Hydroxychloroquine sulfate
NDC: 65841-633 | Form: TABLET, FILM COATED
Manufacturer: Zydus Lifesciences Limited
Category: prescription | Type: HUMAN PRESCRIPTION DRUG LABEL
Date: 20251004

ACTIVE INGREDIENTS: HYDROXYCHLOROQUINE SULFATE 200 mg/1 1
INACTIVE INGREDIENTS: DIBASIC CALCIUM PHOSPHATE DIHYDRATE; MAGNESIUM STEARATE; POLYETHYLENE GLYCOL, UNSPECIFIED; POLYVINYL ALCOHOL, UNSPECIFIED; TALC; TITANIUM DIOXIDE; STARCH, CORN

Hydroxychloroquine sulfate tablets, USP

PACKAGE LABEL.PRINCIPAL DISPLAY PANEL

NDC 65841-633-01 in bottle of 100 tablets

Hydroxychloroquine Sulfate Tablets USP, 200 mg

Rx only

100 tablets